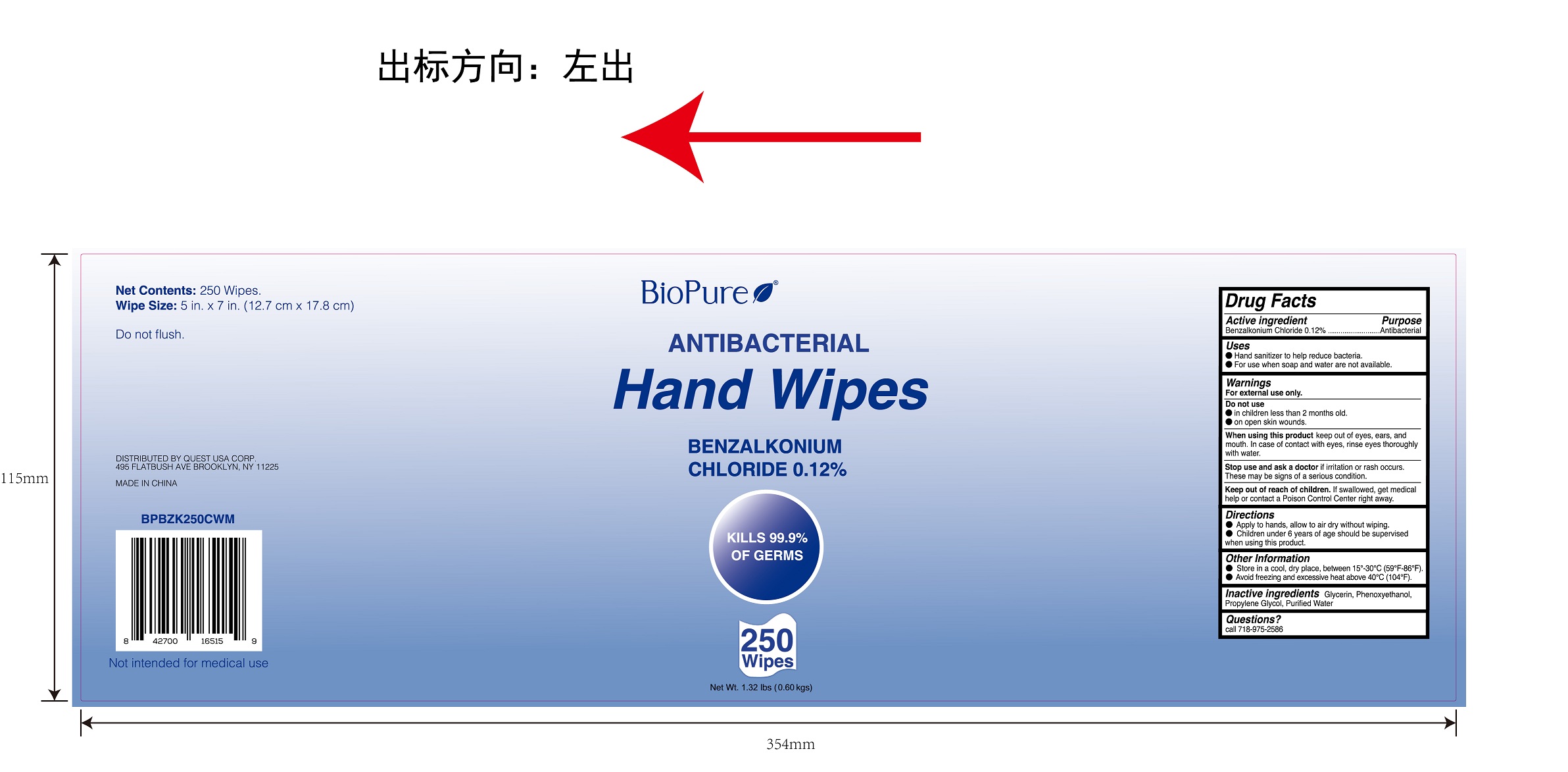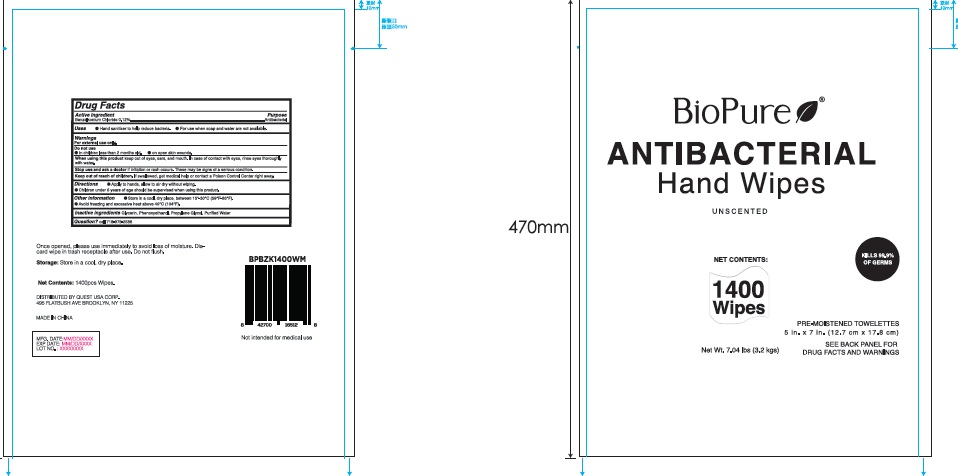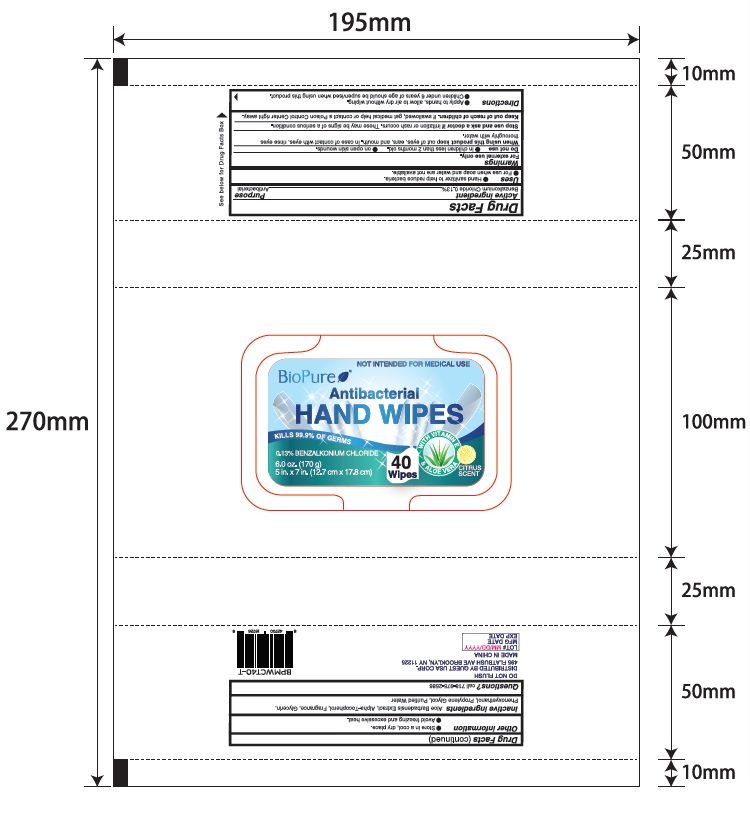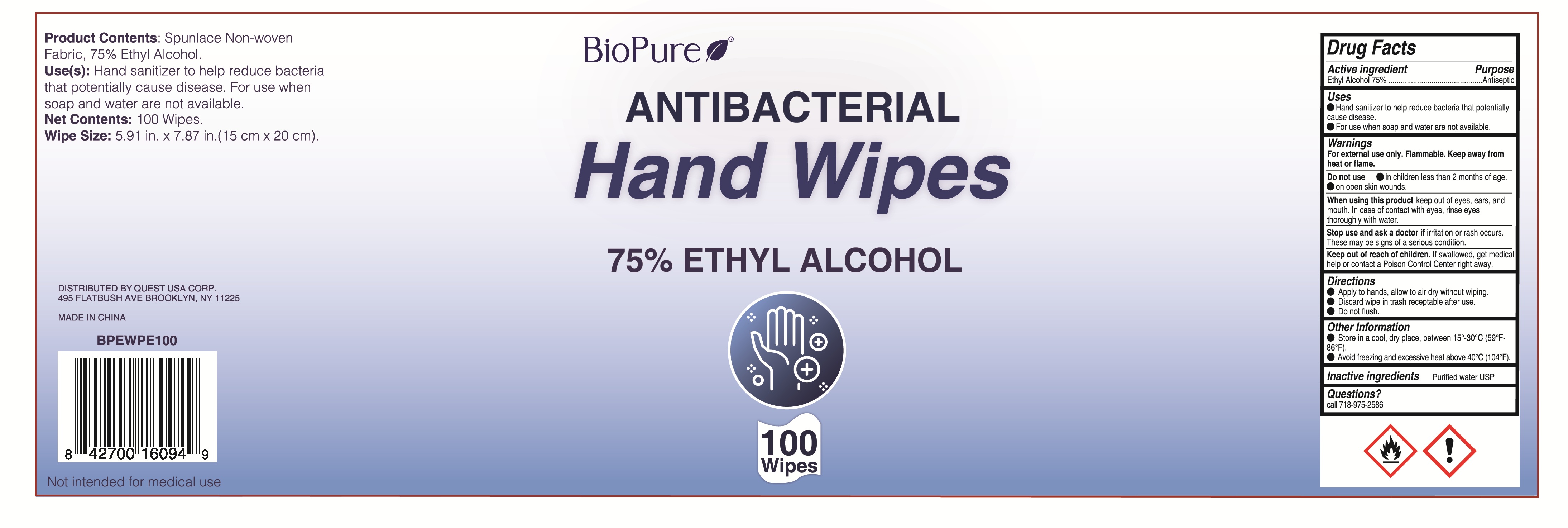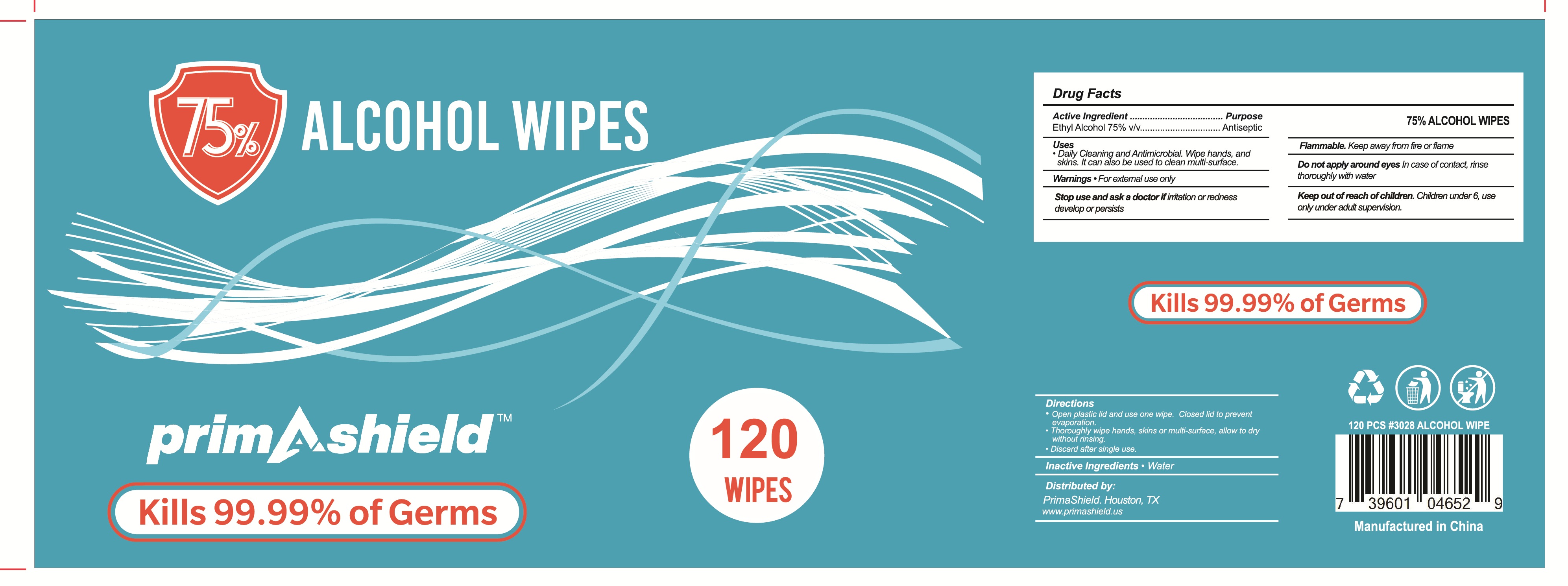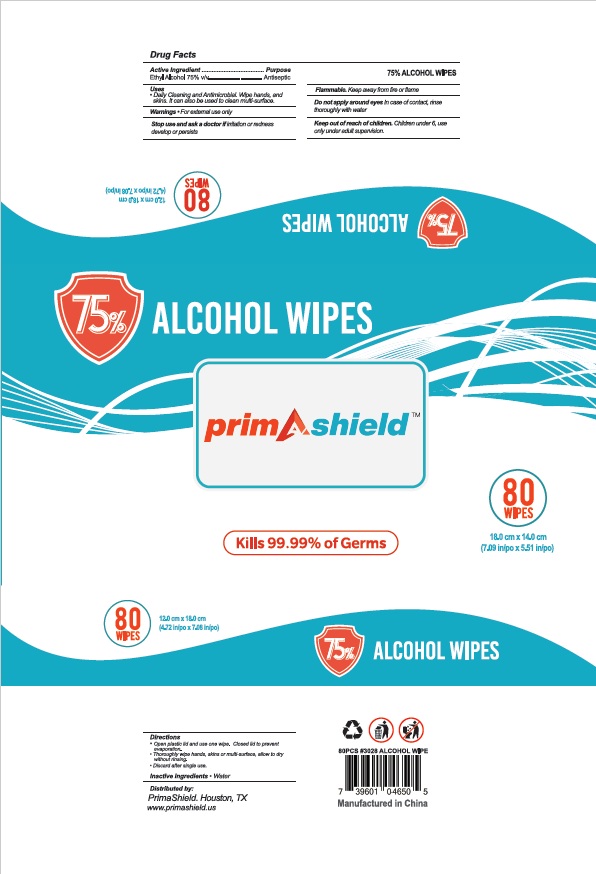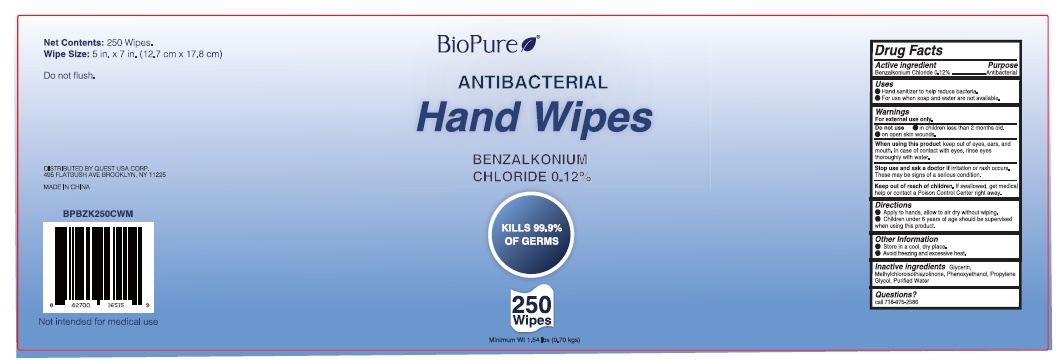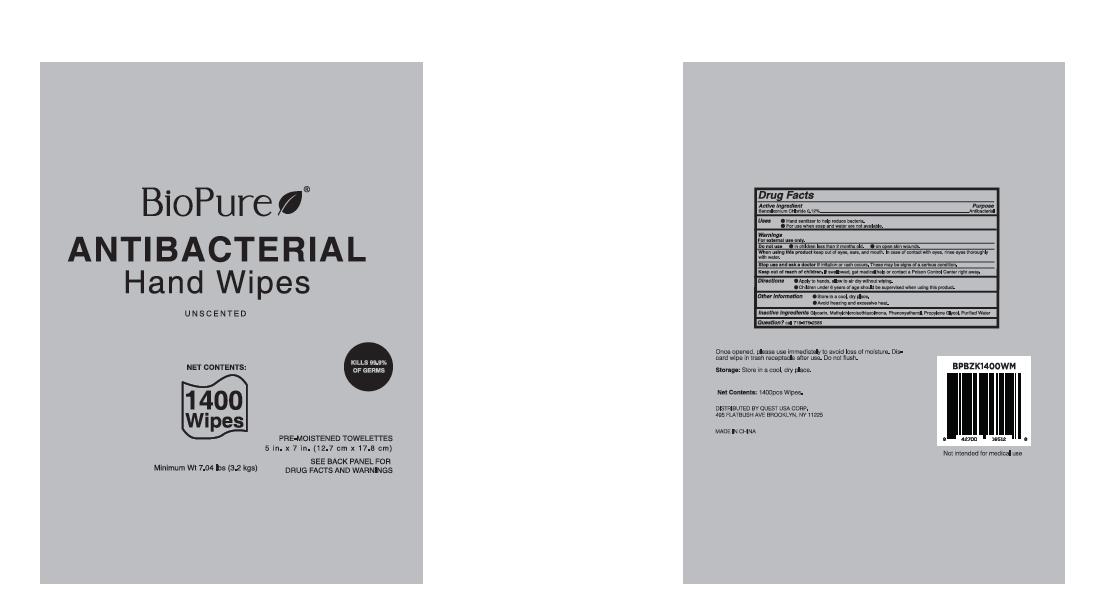 DRUG LABEL: Biopure Antibacterial Hand Wipe  0.12% Benzalkonim Chloride (250 ct)
NDC: 79794-500 | Form: CLOTH
Manufacturer: Zhejiang Furuisen Spunlaced Nonwovens Co., Ltd.
Category: otc | Type: HUMAN OTC DRUG LABEL
Date: 20211019

ACTIVE INGREDIENTS: BENZALKONIUM CHLORIDE 12 1/100 1
INACTIVE INGREDIENTS: PROPYLENE GLYCOL; GLYCERIN; WATER; PHENOXYETHANOL

ACTIVE INGREDIENT

Ethyl Alcohol 75%………………Antisepetic

INACTIVE INGREDIENT

Purified Water USP

WARNINGS

For external use only. Flammable. Keep away from heat or flame.

Keep out of reach of children. If swallowed, get medical help or contact a Poison Control Center right away.

Do not use in children less than 2 months of age.

Do not use on open wounds.

DOSAGE AND ADMINISTRATION

Apply to hands, allow to air dry without wipping.

Discard wipe in trash receptable after use.

Do not flush.

PURPOSE

To help reduce bacteria that potentially cause disease.

INDICATIONS AND USAGE

To help reduce bacteria that potentially cause disease